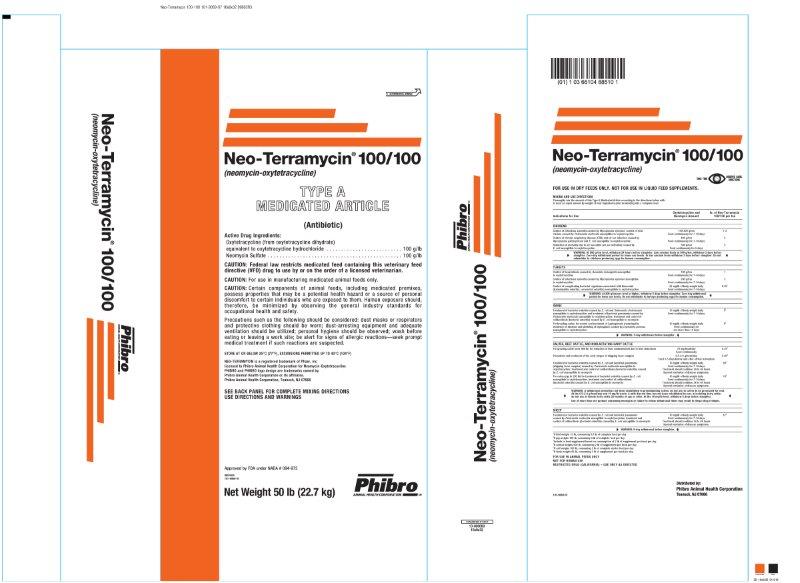 DRUG LABEL: Neo-Terramycin 100/100
NDC: 66104-8851 | Form: POWDER
Manufacturer: Phibro Animal Health
Category: animal | Type: VFD TYPE A MEDICATED ARTICLE ANIMAL DRUG LABEL
Date: 20260121

ACTIVE INGREDIENTS: OXYTETRACYCLINE HYDROCHLORIDE 100 g/0.45 kg; NEOMYCIN SULFATE 100 g/0.45 kg
INACTIVE INGREDIENTS: MINERAL OIL; SODIUM ALUMINOSILICATE; RICE BRAN

Neo-Terramycin® 100/100
(neomycin-oxytetracycline)
TYPE A MEDICATED ARTICLE

(Antibiotic)

Active Drug Ingredients:

Oxytetracycline (from oxytetracycline dihydrate)

equivalent to oxytetracycline hydrochloride . . . . . . . . . . . . . . . . . . . . . . . . . . 100 g/lb

Neomycin Sulfate . . . . . . . . . . . . . . . . . . . . . . . . . . . . . . . . . . . . . . . . . . . . . . 100 g/lb

CAUTION:

CAUTION: Federal law restricts medicated feed containing this veterinary feed directive (VFD) drug to use by or on the order of a licensed veterinarian.

CAUTION: For use in manufacturing medicated animal feeds only.

CAUTION: Certain components of animal feeds, including medicated premixes, possess properties that may be a potential health hazard or a source of personal discomfort to certain individuals who are exposed to them. Human exposure should, therefore, be minimized by observing the general industry standards for occupational health and safety.

Precautions such as the following should be considered: dust masks or respirators and protective clothing should be worn; dust-arresting equipment and adequate ventilation should be utilized; personal hygiene should be observed; wash before eating or leaving a work site; be alert for signs of allergic reactions—seek prompt medical treatment if such reactions are suspected.

STORE IN A DRY, COOL PLACE

STORE AT OR BELOW 25°C (77°F), EXCURSIONS PERMITTED UP TO 40°C (104°F)

MIXING AND USE DIRECTIONS

Thoroughly mix the amount of this Type A Medicated Article according to the directions below withat least an equal amount by weight of feed ingredients prior to blending into a complete feed.

Indications for Use | Oxytetracycline and Neomycin Amount | lb. of Neo-Terramycin 100/100 per ton
CHICKENS
Control of infectious synovitis caused by Mycoplasma synoviae; control of fowl cholera caused by Pasteurella multocida susceptible to oxytetracycline | 100-200 g/ton; Feed continuously for 7-14 days | 1-2
Control of chronic respiratory disease (CRD) and air sac infection caused by Mycoplasma gallisepticum and E. coli susceptible to oxytetracycline | 400 g/ton; Feed continuously for 7-14 days | 4
Reduction of mortality due to air sacculitis (air sac infection) caused by E. coli susceptible to oxytetracycline | 500 g/ton; Feed continuously for 5 days | 5
WARNING: At 500 g/ton level, withdraw 24 hours before slaughter. Low calcium feeds at 500 g/ton, withdraw 3 days before slaughter. Zero-day withdrawal period for lower use levels. In low calcium feeds withdraw 3 days before slaughter. Do not administer to chickens producing eggs for human consumption.
TURKEYS
Control of hexamitiasis caused by Hexamita meleagridis susceptible to oxytetracycline | 100 g/ton; Feed continuously for 7-14 days | 1
Control of infectious synovitis caused by Mycoplasma synoviae susceptible to oxytetracycline | 200 g/ton; Feed continuously for 7-14 days | 2
Control of complicating bacterial organisms associated with bluecomb (transmissible enteritis, coronaviral enteritis) susceptible to oxytetracycline | 25 mg/lb of body weight daily; Feed continuously for 7-14 days | 8.35^1
WARNING: At 200 g/ton use level or higher, withdraw 5 days before slaughter. Zero-day withdrawal period for lower use levels. Do not administer to turkeys producing eggs for human consumption.
SWINE
Treatment of bacterial enteritis caused by E. coli and Salmonella choleraesuis susceptible to oxytetracycline and treatment of bacterial pneumonia caused by Pasteurella multocida susceptible to oxytetracycline; treatment and control of colibacillosis (bacterial enteritis) caused by E. coli susceptible to neomycin | 10 mg/lb of body weight daily; Feed continuously for 7-14 days | 5^2
For breeding swine for control and treatment of Leptospirosis (reducing the incidence of abortion and shedding of leptospirae) caused by Leptospira pomona susceptible to oxytetracycline | 10 mg/lb of body weight daily; Feed continuously for not more than 14 days | 5^2
WARNING: 5-day withdrawal before slaughter at 10 mg/lb dosage.
CALVES, BEEF CATTLE, AND NONLACTATING DAIRY CATTLE
For growing cattle (over 400 lb) for reduction of liver condemnation due to liver abscesses | 75 mg/head/day; Feed continuously | 0.75^3
Prevention and treatment of the early stages of shipping fever complex | 0.5-2.0 g/head/day; Feed 3-5 days before and after arrival in feedlots | 5-20^3
Treatment of bacterial enteritis caused by E. coli and bacterial pneumonia (shipping fever complex) caused by Pasteurella multocida susceptible to oxytetracycline; treatment and control of colibacillosis (bacterial enteritis) caused by E. coli susceptible to neomycin | 10 mg/lb of body weight daily; Feed continuously for 7-14 days; Treatment should continue 24 to 48 hours beyond remission of disease symptoms. | 50^4
For calves (up to 250 lb) for treatment of bacterial enteritis caused by E. coli susceptible to oxytetracycline; treatment and control of colibacillosis (bacterial enteritis) caused by E. coli susceptible to neomycin | 10 mg/lb of body weight daily; Feed continuously for 7-14 days; Treatment should continue 24 to 48 hours beyond remission of disease symptoms. | 10^5
WARNING: A withdrawal period has not been established in preruminating calves; do not use in calves to be processed for veal. At the 0.5-2.0 g/head/day and 10 mg/lb levels: A milk discard time has not been established for use in lactating dairy cattle; do not use in female dairy cattle 20 months of age or older. At the 10 mg/lb level, withdraw 5 days before slaughter. Use of more than one product containing neomycin or failure to follow withdrawal times may result in illegal drug residues.
SHEEP
Treatment of bacterial enteritis caused by E. coli and bacterial pneumonia caused by Pasteurella multocida susceptible to oxytetracycline; treatment and control of colibacillosis (bacterial enteritis) caused by E. coli susceptible to neomycin | 10 mg/lb of body weight daily; Feed continuously for 7-14 days; Treatment should continue 24 to 48 hours beyond remission of disease symptoms. | 12^6
WARNING: 5-day withdrawal before slaughter at 10 mg/lb dosage.
^1If bird weighs 10 lb, consuming 0.6 lb of complete feed per day
^2If pig weighs 100 lb, consuming 4 lb of complete feed per day
^3Include in feed supplement based on consumption of 2 lb of supplement per head per day
^4If animal weighs 500 lb, consuming 2 lb of supplement per head per day
^5If calf weighs 100 lb, consuming 2 lb of complete starter feed per day
^6If lamb weighs 60 lb, consuming 1 lb of supplement per head per day

INDICATIONS AND USAGE

FOR USE IN ANIMAL FEEDS ONLY

NOT FOR HUMAN USE

RESTRICTED DRUG (CALIFORNIA) – USE ONLY AS DIRECTED

NEO-TERRAMYCIN is a registered trademark of Pfizer, Inc

licensed to Phibro Animal Health Corporation for Neomycin-Oxytetracycline

PHIBRO and PHIBRO logo design are trademarks owned by

Phibro Animal Health Corporation or its affiliates.

Phibro Animal Health Corporation, Teaneck, NJ 07666

SEE BACK PANEL FOR COMPLETE MIXING DIRECTIONS

USE DIRECTIONS AND WARNINGS

Net Weight 50 lb (22.7 kg)

Approved by FDA under NADA # 094-975

8851000

101-9069-07

Neo-Terramycin 100-100 Label

Label